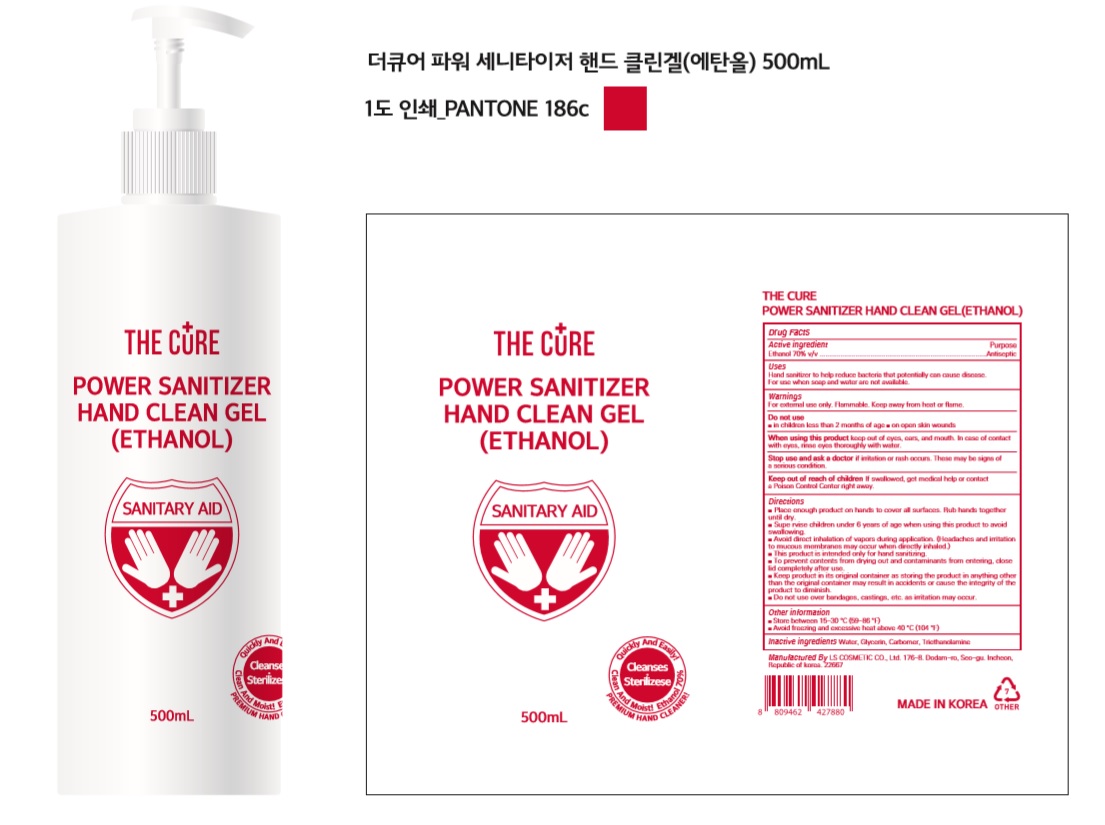 DRUG LABEL: THE CURE POWER SANITIZER HAND CLEAN Gel(Ethanol)
NDC: 59545-0570 | Form: GEL
Manufacturer: LS COSMETIC CO.,LTD.
Category: otc | Type: HUMAN OTC DRUG LABEL
Date: 20200413

ACTIVE INGREDIENTS: ALCOHOL 350 mL/500 mL
INACTIVE INGREDIENTS: GLYCERIN; CARBOMER HOMOPOLYMER, UNSPECIFIED TYPE; WATER; TROLAMINE

THE CURE POWER SANITIZER HAND CLEAN Gel(Ethanol) : 59545-0570